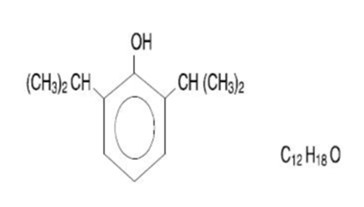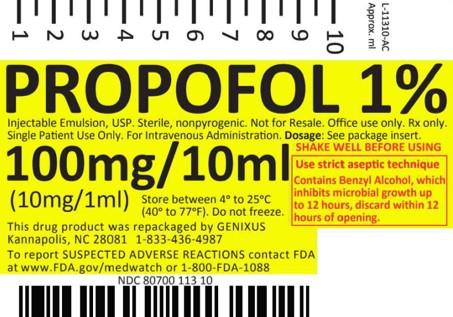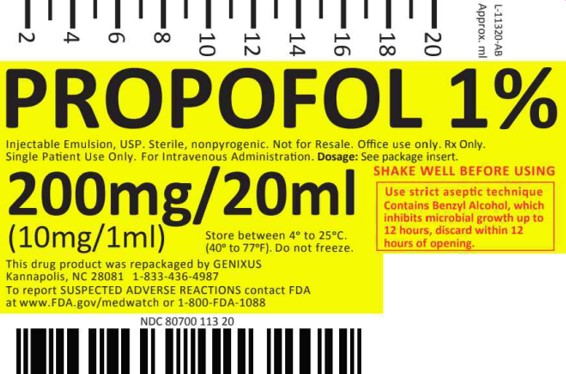 DRUG LABEL: Propofol 1%
NDC: 80700-113 | Form: INJECTION, EMULSION
Manufacturer: Genixus
Category: prescription | Type: HUMAN PRESCRIPTION DRUG LABEL
Date: 20231227

ACTIVE INGREDIENTS: PROPOFOL 10 mg/1 mL
INACTIVE INGREDIENTS: GLYCERIN 22.5 mg/1 mL; SOYBEAN OIL 100 mg/1 mL; EGG PHOSPHOLIPIDS 12 mg/1 mL; BENZYL ALCOHOL 0.0015 mg/1 mL

DESCRIPTION

Propofol injectable emulsion, USP is a sterile, nonpyrogenic white or almost white, homogeneous
emulsion, containing 10 mg/mL of propofol, USP suitable for intravenous administration. Propofol,
USP is chemically described as 2,6-diisopropylphenol and has a molecular weight of 178.27.
The structural formula is:

Propofol, USP is slightly soluble in water and, thus, is formulated in a white, oil-in-water emulsion.
The pKa is 11. The octanol/water partition coefficient for propofol, USP is 6761:1 at a pH of 4.5 to
7.4. In addition to the active component, propofol, USP the formulation also contains
soybean oil (100 mg/mL), glycerol (22.5 mg/mL), egg phospholipids (12 mg/mL); and benzyl alcohol
(0.15%); with sodium hydroxide to adjust pH. Propofol injectable emulsion, USP is isotonic and has
a pH of 5.5 to 7.4.